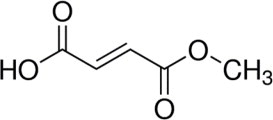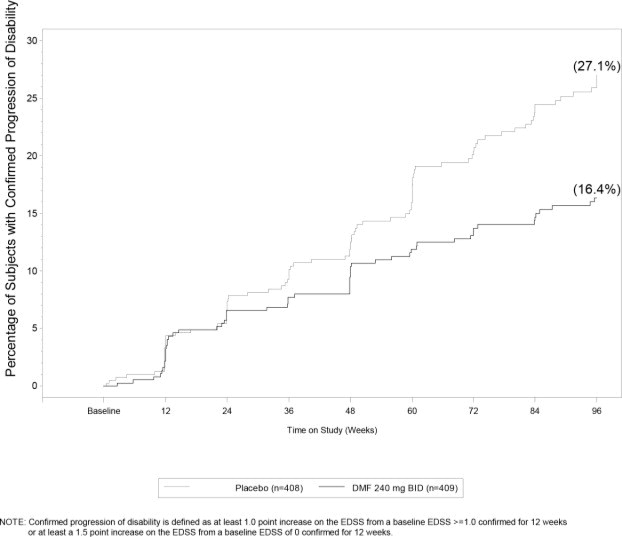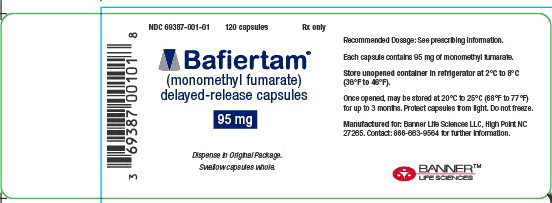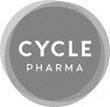 DRUG LABEL: BAFIERTAM

NDC: 69387-001 | Form: CAPSULE
Manufacturer: Banner Life Sciences LLC

Category: prescription | Type: HUMAN PRESCRIPTION DRUG LABEL
Date: 20250905

ACTIVE INGREDIENTS: MONOMETHYL FUMARATE 95 mg/1 1
INACTIVE INGREDIENTS: GLYCERYL CAPRYLATE/CAPRATE; GLYCERYL MONO- AND DICAPRYLOCAPRATE; POVIDONE K30; POLYOXYL 40 HYDROGENATED CASTOR OIL; Lactic Acid, Unspecified Form; gelatin, unspecified; Titanium Dioxide; Hypromellose 2910 (6 MPA.S); polyethylene glycol 400; Polyvinyl Alcohol, Unspecified; talc; Sodium Lauryl Sulfate; Sorbitan; Sorbitol; Shellac; Isopropyl Alcohol; Ferrosoferric Oxide; Butyl Alcohol; Propylene glycol; Methacrylic Acid - Ethyl Acrylate Copolymer (1:1) Type A; Triethyl Citrate; SILICON DIOXIDE; SODIUM BICARBONATE; AMMONIA

HIGHLIGHTS OF PRESCRIBING INFORMATION

These highlights do not include all the information needed to use BAFIERTAM safely and effectively. See full prescribing information for BAFIERTAM.
BAFIERTAM® (monomethyl fumarate) delayed-release capsules, for oral use
Initial U.S. Approval: 2013

1 INDICATIONS AND USAGE

BAFIERTAM is indicated for the treatment of relapsing forms of multiple sclerosis (MS), to include clinically isolated syndrome, relapsing-remitting disease, and active secondary progressive disease, in adults. (1)

2 DOSAGE AND ADMINISTRATION

- Blood tests are required prior to initiation of BAFIERTAM. (2.1)
- Starting dose: 95 mg twice a day, orally, for 7 days (2.2)
- Maintenance dose after 7 days: 190 mg (administered as two 95 mg capsules) twice a day, orally (2.2)
- Swallow BAFIERTAM capsules whole and intact. Do not crush, chew, or mix contents with food. (2.3)
- Take BAFIERTAM with or without food. (2.3)

3 DOSAGE FORMS AND STRENGTHS

Delayed-release capsules: 95 mg (3)

4 CONTRAINDICATIONS

- Known hypersensitivity to monomethyl fumarate, dimethyl fumarate, diroximel fumarate, or any of the excipients of BAFIERTAM
- Co-administration with dimethyl fumarate or diroximel fumarate (4)

5 WARNINGS AND PRECAUTIONS

- Anaphylaxis and Angioedema: Discontinue and do not restart BAFIERTAM if these occur. (5.1)
- Progressive Multifocal Leukoencephalopathy (PML): Withhold BAFIERTAM at the first sign or symptom suggestive of PML. (5.2)
- Herpes Zoster and Other Serious Opportunistic Infections: Consider withholding BAFIERTAM in cases of serious infection until the infection has resolved. (5.3)
- Lymphopenia: Obtain a CBC including lymphocyte count before initiating BAFIERTAM, after 6 months, and every 6 to 12 months thereafter. Consider interruption of BAFIERTAM if lymphocyte counts <0.5 x 10^9/L persist for more than six months. (5.4)
- Liver Injury: Obtain serum aminotransferase, alkaline phosphatase, and total bilirubin levels before initiating BAFIERTAM and during treatment, as clinically indicated. Discontinue BAFIERTAM if clinically significant liver injury induced by BAFIERTAM is suspected. (5.5)

6 ADVERSE REACTIONS

Most common adverse reactions (incidence for dimethyl fumarate [the prodrug of BAFIERTAM] ≥10% and ≥2% more than placebo) were flushing, abdominal pain, diarrhea, and nausea. (6.1)

To report SUSPECTED ADVERSE REACTIONS, contact Banner Life Sciences at toll-free phone: 1-866-MMF- 95MG or FDA at 1-800-FDA-1088 or www.fda.gov/medwatch.

8 USE IN SPECIFIC POPULATIONS

- Pregnancy: Based on animal data, may cause fetal harm. (8.1)

FULL PRESCRIBING INFORMATION

1 INDICATIONS AND USAGE

BAFIERTAM is indicated for the treatment of relapsing forms of multiple sclerosis (MS), to include clinically isolated syndrome, relapsing-remitting disease, and active secondary progressive disease, in adults.

2 DOSAGE AND ADMINISTRATION

2.1 Blood Tests Prior to Initiation of BAFIERTAM

Obtain the following prior to treatment with BAFIERTAM:

- A complete blood cell count (CBC), including lymphocyte count [see Warnings and Precautions (5.4)].
- Serum aminotransferase, alkaline phosphatase, and total bilirubin levels [see Warnings and Precautions (5.5)].

2.2 Dosing Information

The starting dosage for BAFIERTAM is 95 mg twice a day orally for 7 days. After 7 days, the dosage should be increased to the maintenance dosage of 190 mg (administered as two 95 mg capsules) twice a day orally. Temporary dosage reductions to 95 mg twice a day may be considered for individuals who do not tolerate the maintenance dosage. Within 4 weeks, the recommended dosage of 190 mg twice a day should be resumed. Discontinuation of BAFIERTAM should be considered for patients unable to tolerate return to the maintenance dosage. Administration of non-enteric coated aspirin (up to a dose of 325 mg) 30 minutes prior to BAFIERTAM dosing may reduce the incidence or severity of flushing [see Clinical Pharmacology (12.3)].

2.3 Administration Instructions

Swallow BAFIERTAM capsules whole and intact. Do not crush, chew, or mix the contents with food. BAFIERTAM can be taken with or without food.

2.4 Blood Tests to Assess Safety After Initiation of BAFIERTAM

Obtain a complete blood cell count (CBC), including lymphocyte count, 6 months after initiation of BAFIERTAM and then every 6 to 12 months thereafter, as clinically indicated [see Warnings and Precautions (5.3)].

Obtain serum aminotransferase, alkaline phosphatase, and total bilirubin levels during treatment with BAFIERTAM, as clinically indicated [see Warnings and Precautions (5.4)].

3 DOSAGE FORMS AND STRENGTHS

BAFIERTAM is available as soft gelatin delayed-release capsules containing 95 mg of monomethyl fumarate. The 95 mg capsule is white, opaque, oval, coated, and printed with “95” in black ink on the body.

4 CONTRAINDICATIONS

BAFIERTAM is contraindicated in patients:

- with known hypersensitivity to monomethyl fumarate, dimethyl fumarate, diroximel fumarate, or to any of the excipients of BAFIERTAM. Reactions may include anaphylaxis or angioedema [see Warnings and Precautions (5.1)].
- taking dimethyl fumarate or diroximel fumarate [see Drug Interactions (7.1)].

5 WARNINGS AND PRECAUTIONS

5.1 Anaphylaxis and Angioedema

BAFIERTAM can cause anaphylaxis and angioedema after the first dose or at any time during treatment. Signs and symptoms in patients taking dimethyl fumarate (the prodrug of BAFIERTAM) have included difficulty breathing, urticaria, and swelling of the throat and tongue. Patients should be instructed to discontinue BAFIERTAM and seek immediate medical care should they experience signs and symptoms of anaphylaxis or angioedema.

5.2 Progressive Multifocal Leukoencephalopathy

Progressive multifocal leukoencephalopathy (PML) has occurred in patients with MS treated with dimethyl fumarate (the prodrug of BAFIERTAM). PML is an opportunistic viral infection of the brain caused by the JC virus (JCV) that typically only occurs in patients who are immunocompromised, and that usually leads to death or severe disability. A fatal case of PML occurred in a patient who received dimethyl fumarate for 4 years while enrolled in a clinical trial. During the clinical trial, the patient experienced prolonged lymphopenia (lymphocyte counts predominantly <0.5x10^9/L for 3.5 years) while taking dimethyl fumarate [see Warnings and Precautions (5.4)]. The patient had no other identified systemic medical conditions resulting in compromised immune system function and had not previously been treated with natalizumab, which has a known association with PML. The patient was also not taking any immunosuppressive or immunomodulatory medications concomitantly.

PML has also occurred in patients taking dimethyl fumarate in the postmarketing setting in the presence of lymphopenia (<0.9x10^9/L). While the role of lymphopenia in these cases is uncertain, the PML cases have occurred predominantly in patients with lymphocyte counts <0.8x10^9/L persisting for more than 6 months.

At the first sign or symptom suggestive of PML, withhold BAFIERTAM and perform an appropriate diagnostic evaluation. Typical symptoms associated with PML are diverse, progress over days to weeks, and include progressive weakness on one side of the body or clumsiness of limbs, disturbance of vision, and changes in thinking, memory, and orientation leading to confusion and personality changes.

Magnetic resonance imaging (MRI) findings may be apparent before clinical signs or symptoms. Cases of PML, diagnosed based on MRI findings and the detection of JCV DNA in the cerebrospinal fluid in the absence of clinical signs or symptoms specific to PML, have been reported in patients treated with other MS medications associated with PML. Many of these patients subsequently became symptomatic with PML. Therefore, monitoring with MRI for signs that may be consistent with PML may be useful, and any suspicious findings should lead to further investigation to allow for an early diagnosis of PML, if present. Lower PML-related mortality and morbidity have been reported following discontinuation of another MS medication associated with PML in patients with PML who were initially asymptomatic compared to patients with PML who had characteristic clinical signs and symptoms at diagnosis. It is not known whether these differences are due to early detection and discontinuation of MS treatment or due to differences in disease in these patients.

5.3 Herpes Zoster and Other Serious Opportunistic Infections

Serious cases of herpes zoster have occurred with dimethyl fumarate (the prodrug of BAFIERTAM), including disseminated herpes zoster, herpes zoster ophthalmicus, herpes zoster meningoencephalitis, and herpes zoster meningomyelitis. These events may occur at any time during treatment. Monitor patients on BAFIERTAM for signs and symptoms of herpes zoster. If herpes zoster occurs, appropriate treatment for herpes zoster should be administered.

Other serious opportunistic infections have occurred with dimethyl fumarate, including cases of serious viral (herpes simplex virus, West Nile virus, cytomegalovirus), fungal (Candida and Aspergillus), and bacterial (Nocardia, Listeria monocytogenes, Mycobacterium tuberculosis) infections. These infections have been reported in patients with reduced absolute lymphocyte counts (ALC) as well as in patients with normal ALC. These infections have affected the brain, meninges, spinal cord, gastrointestinal tract, lungs, skin, eye, and ear. Patients with symptoms and signs consistent with any of these infections should undergo prompt diagnostic evaluation and receive appropriate treatment.

Consider withholding BAFIERTAM treatment in patients with herpes zoster or other serious infections until the infection has resolved [see Adverse Reactions (6.2)].

5.4 Lymphopenia

BAFIERTAM may decrease lymphocyte counts. In the MS placebo-controlled trials with dimethyl fumarate (the prodrug of BAFIERTAM), mean lymphocyte counts decreased by approximately 30% during the first year of treatment with dimethyl fumarate and then remained stable. Four weeks after stopping dimethyl fumarate, mean lymphocyte counts increased, but did not return to baseline. Six percent (6%) of dimethyl fumarate patients and <1% of placebo patients experienced lymphocyte counts <0.5x10^9/L (lower limit of normal 0.91x10^9/L). The incidence of infections (60% vs 58%) and serious infections (2% vs 2%) was similar in patients treated with dimethyl fumarate or placebo, respectively. There was no increased incidence of serious infections observed in patients with lymphocyte counts <0.8x10^9/L or ≤0.5x10^9/L in controlled trials, although one patient in an extension study developed PML in the setting of prolonged lymphopenia (lymphocyte counts predominantly <0.5x10^9/L for 3.5 years) [see Warnings and Precautions (5.2)].

In controlled and uncontrolled clinical trials with dimethyl fumarate, 2% of patients experienced prolonged, severe lymphopenia (defined as lymphocyte counts <0.5x10^9/L for at least six months); in this group of patients, the majority of lymphocyte counts remained <0.5x10^9/L with continued therapy. In these patients with prolonged, severe lymphopenia, the median time for lymphocyte counts to return to normal after discontinuing dimethyl fumarate was 96.0 weeks.

In these controlled and uncontrolled clinical studies, among patients who did not experience prolonged, severe lymphopenia during treatment, the median times for lymphocyte counts to return to normal after discontinuing dimethyl fumarate were as follows:

- 4.3 weeks in patients with mild lymphopenia (lymphocyte count ≥0.8x10^9/L) at discontinuation,
- 10.0 weeks in patients with moderate lymphopenia (lymphocyte count 0.5 to <0.8x10^9/L) at discontinuation, and
- 16.7 weeks in patients with severe lymphopenia (lymphocyte count <0.5x10^9/L) at discontinuation.

Neither BAFIERTAM nor dimethyl fumarate have been studied in patients with preexisting low lymphocyte counts.

Obtain a CBC, including lymphocyte count, before initiating treatment with BAFIERTAM, 6 months after starting treatment, and then every 6 to 12 months thereafter, and as clinically indicated. Consider interruption of BAFIERTAM in patients with lymphocyte counts less than 0.5x10^9/L persisting for more than six months. Given the potential for delayed recovery of lymphocyte counts, continue to obtain lymphocyte counts until their recovery if BAFIERTAM is discontinued or interrupted because of lymphopenia. Consider withholding treatment from patients with serious infections until resolution. Decisions about whether or not to restart BAFIERTAM should be individualized based on clinical circumstances.

5.5 Liver Injury

Clinically significant cases of liver injury have been reported in patients treated with dimethyl fumarate (the prodrug of BAFIERTAM) in the postmarketing setting. The onset has ranged from a few days to several months after initiation of treatment with dimethyl fumarate. Signs and symptoms of liver injury, including elevation of serum aminotransferases to greater than 5-fold the upper limit of normal and elevation of total bilirubin to greater than 2-fold the upper limit of normal have been observed. These abnormalities resolved upon treatment discontinuation. Some cases required hospitalization. None of the reported cases resulted in liver failure, liver transplant, or death. However, the combination of new serum aminotransferase elevations with increased levels of bilirubin caused by drug-induced hepatocellular injury is an important predictor of serious liver injury that may lead to acute liver failure, liver transplant, or death in some patients.

Elevations of hepatic transaminases (most no greater than 3 times the upper limit of normal) were observed during controlled trials with dimethyl fumarate [see Adverse Reactions (6.1)].

Obtain serum aminotransferase, alkaline phosphatase (ALP), and total bilirubin levels prior to treatment with BAFIERTAM and during treatment, as clinically indicated. Discontinue BAFIERTAM if clinically significant liver injury induced by BAFIERTAM is suspected.

5.6 Flushing

BAFIERTAM may cause flushing (e.g., warmth, redness, itching, and/or burning sensation). In clinical trials of dimethyl fumarate (the prodrug of BAFIERTAM), 40% of dimethyl fumarate treated patients experienced flushing. Flushing symptoms generally began soon after initiating dimethyl fumarate and usually improved or resolved over time. In the majority of patients who experienced flushing, it was mild or moderate in severity. Three percent (3%) of patients discontinued dimethyl fumarate for flushing, and <1% had serious flushing symptoms that were not life-threatening but led to hospitalization. Studies with dimethyl fumarate show that administration of non-enteric coated aspirin (up to a dose of 325 mg) 30 minutes prior to dosing may reduce the incidence or severity of flushing [see Clinical Pharmacology (12.3)]. In the BAFIERTAM studies, the presence of food did not impact the incidence of flushing.

5.7 Serious Gastrointestinal Reactions

Serious gastrointestinal reactions, including perforation, ulceration, hemorrhage, and obstruction, some with fatal outcomes, have been reported in the postmarketing setting with the use of fumaric acid esters, including dimethyl fumarate, with or without concomitant aspirin use. The majority of these events have occurred within 6 months of fumaric acid ester treatment initiation. In controlled clinical trials, the incidence of serious gastrointestinal adverse events was 1% in patients treated with dimethyl fumarate; these events, none of which were fatal, included vomiting (0.3%) and abdominal pain (0.3%) [see Adverse Reactions (6.1)].

Monitor patients, promptly evaluate, and discontinue BAFIERTAM for new or worsening severe gastrointestinal signs and symptoms.

6 ADVERSE REACTIONS

The following clinically significant adverse reactions are described elsewhere in the labeling:

- Anaphylaxis and Angioedema [see Warnings and Precautions (5.1)]
- Progressive Multifocal Leukoencephalopathy [see Warnings and Precautions (5.2)]
- Herpes Zoster and Other Serious Opportunistic Infections [see Warnings and Precautions (5.3)]
- Lymphopenia [see Warnings and Precautions (5.4)]
- Liver Injury [see Warnings and Precautions (5.5)]
- Flushing [see Warnings and Precautions (5.6)]
- Serious Gastrointestinal Reactions [see Warnings and Precautions (5.7)]

6.1 Clinical Trials Experience

Because clinical trials are conducted under widely varying conditions, adverse reaction rates observed in the clinical trials of a drug cannot be directly compared to rates in the clinical trials of another drug and may not reflect the rates observed in practice.

The data described in the following sections were obtained using dimethyl fumarate delayed-release capsules (the prodrug of BAFIERTAM).

Adverse Reactions in Placebo-Controlled Trials with Dimethyl Fumarate

In the two well-controlled studies demonstrating effectiveness, 1529 patients received dimethyl fumarate with an overall exposure of 2244 person-years [see Clinical Studies (14)]. The adverse reactions presented in Table 1 below are based on safety information from 769 patients treated with dimethyl fumarate 240 mg twice a day and 771 placebo-treated patients. The most common adverse reactions (incidence ≥10% and ≥2% more than placebo) for dimethyl fumarate were flushing, abdominal pain, diarrhea, and nausea.

Table 1: Adverse Reactions in Study 1 and 2 Reported for Dimethyl Fumarate at ≥ 2% Higher Incidence than Placebo
Adverse Reaction | Dimethyl Fumarate 240 mg Twice Daily N=769 % | Placebo N=771 %
Flushing | 40 | 6
Abdominal pain | 18 | 10
Diarrhea | 14 | 11
Nausea | 12 | 9
Vomiting | 9 | 5
Pruritus | 8 | 4
Rash | 8 | 3
Albumin urine present | 6 | 4
Erythema | 5 | 1
Dyspepsia | 5 | 3
Aspartate aminotransferase increased | 4 | 2
Lymphopenia | 2 | <1

Gastrointestinal

Dimethyl fumarate caused GI events (e.g., nausea, vomiting, diarrhea, abdominal pain, and dyspepsia). In clinical trials, the incidence of GI events was higher early in the course of treatment (primarily during the first month) and usually decreased over time in patients treated with dimethyl fumarate compared with placebo. Four percent (4%) of patients treated with dimethyl fumarate and less than 1% of patients on placebo discontinued due to gastrointestinal events. The incidence of serious GI events was 1% in clinical trial patients treated with dimethyl fumarate; these events, none of which were fatal, included vomiting (0.3%) and abdominal pain (0.3%).

Hepatic Transaminases

An increased incidence of elevations of hepatic transaminases in patients treated with dimethyl fumarate in clinical trials was seen primarily during the first six months of treatment, and most patients with elevations had levels < 3 times the upper limit of normal (ULN). Elevations of alanine aminotransferase and aspartate aminotransferase to ≥ 3 times the ULN occurred in a small number of patients treated with both dimethyl fumarate and in patients on placebo, and were balanced between the groups. There were no elevations in transaminases ≥ 3 times the ULN with concomitant elevations in total bilirubin > 2 times the ULN. Discontinuations due to elevated hepatic transaminases were < 1%, and were similar in patients treated with dimethyl fumarate or placebo.

Eosinophilia

A transient increase in mean eosinophil counts was seen during the first 2 months of therapy with dimethyl fumarate.

Adverse Reactions in Studies with BAFIERTAM (Monomethyl Fumarate)

In clinical studies, a total of 178 healthy subjects have received single doses of BAFIERTAM. The adverse reaction profile of BAFIERTAM was consistent with the experience in the placebo-controlled clinical trials with dimethyl fumarate. Taking BAFIERTAM without food may reduce the incidence of GI events.

6.2 Postmarketing Experience

The following adverse reactions have been identified during post approval use of dimethyl fumarate (the prodrug of BAFIERTAM). Because these reactions are reported voluntarily from a population of uncertain size, it is not always possible to reliably estimate their frequency or establish a causal relationship to drug exposure.

Gastrointestinal Disorders: Acute pancreatitis; Gastrointestinal perforation, ulceration, obstruction, and hemorrhage [see Warnings and Precautions (5.7)]

Hepatobiliary Disorders: Liver function abnormalities (elevations in transaminases ≥ 3 times

ULN with concomitant elevations in total bilirubin > 2 times ULN) [see Warnings and Precautions (5.5)]

Infections and Infestations: Herpes zoster infection and other serious opportunistic infections [see Warnings and Precautions (5.3)]

Respiratory, Thoracic, and Mediastinal Disorders: Rhinorrhea

Skin and Subcutaneous: Alopecia

7 DRUG INTERACTIONS

7.1 Concomitant Dimethyl Fumarate or Diroximel Fumarates

Both dimethyl fumarate and diroximel fumarate are metabolized to monomethyl fumarate. Therefore, BAFIERTAM is contraindicated in patients currently taking dimethyl fumarate or diroximel fumarate. BAFIERTAM may be initiated the day following discontinuation of either of these drugs.

8 USE IN SPECIFIC POPULATIONS

8.1 Pregnancy

Pregnancy Exposure Registry

There is a pregnancy exposure registry that monitors pregnancy outcomes in women exposed to BAFIERTAM during pregnancy. Pregnant women exposed to BAFIERTAM and healthcare providers are encouraged to contact Banner Life Sciences at 1-866-MMF-95MG (1-866-663-9564).

Risk Summary

There are no adequate data on the developmental risk associated with the use of BAFIERTAM in pregnant women.
Available data from a pregnancy registry for dimethyl fumarate (the prodrug of BAFIERTAM), observational studies, and pharmacovigilance with dimethyl fumarate use in pregnant women have not indicated an increased risk of major birth defects, miscarriage, or other adverse maternal or fetal outcomes. Most of the reported exposures to dimethyl fumarate occurred during the first trimester of pregnancy (see Data).
In animals, adverse effects on offspring survival, growth, sexual maturation, and neurobehavioral function were observed when dimethyl fumarate (DMF) was administered during pregnancy and lactation at clinically relevant doses (see Data).

The background risk of major birth defects and miscarriage for the indicated population is unknown. All pregnancies have a background risk of birth defect, loss, or other adverse outcomes. In the U.S. general population, the estimated background risk of major birth defects and miscarriage in clinically recognized pregnancies is 2-4% and 15-20%, respectively.

Data

Human Data

In a prospective observational pregnancy registry for dimethyl fumarate (2013-2022), the rate of major birth defects among 362 live births and stillbirths from women who were exposed to dimethyl fumarate during pregnancy was 3.6% (95% CI: 1.9-6.1). No specific pattern of major birth defects was identified. Important potential study limitations include exposure misclassification, no adjustment for confounders, and lack of an internal comparator cohort.

Animal data

In rats administered DMF orally (0, 25, 100, and 250 mg/kg/day) throughout organogenesis, embryofetal toxicity (reduced fetal body weight and delayed ossification) were observed at the highest dose tested. This dose also produced evidence of maternal toxicity (reduced body weight). Plasma exposure (AUC) for monomethyl fumarate (MMF), the major circulating metabolite, at the no-effect dose is approximately three times that in humans at the recommended human dose (RHD) of MMF (380 mg/day). In rabbits administered DMF orally (0, 25, 75, and 150 mg/kg/day) throughout organogenesis, embryolethality and decreased maternal body weight were observed at the highest dose tested. The plasma AUC for MMF at the no-effect dose is approximately 5 times that in humans at the RHD of MMF.

Oral administration of DMF (0, 25, 100, and 250 mg/kg/day) to rats throughout organogenesis and lactation resulted in increased lethality, persistent reductions in body weight, delayed sexual maturation (male and female pups), and reduced testicular weight at the highest dose tested. Neurobehavioral impairment was observed at all doses. A no-effect dose for developmental toxicity was not identified. The lowest dose tested was associated with plasma AUC for MMF lower than that in humans at the RHD of MMF.

8.2 Lactation

Risk Summary

There are no data on the presence of DMF or MMF in human milk. The effects on the breastfed infant and on milk production are unknown.

The developmental and health benefits of breastfeeding should be considered along with the mother's clinical need for BAFIERTAM and any potential adverse effects on the breastfed infant from the drug or from the underlying maternal condition.

8.4 Pediatric Use

Safety and effectiveness in pediatric patients have not been established.

Juvenile Animal Toxicity Data

Oral administration of monomethyl fumarate (MMF) (0, 40, 100, or 250 mg/kg/day) to juvenile rats from postnatal day 28 to 70 resulted in reduced body weight and bone growth, delayed sexual maturation in females, and renal tubular (exfoliated cells or degeneration) and gastrointestinal (nonglandular stomach hyperkeratosis or hyperplasia) effects at all but the lowest dose tested. No adverse effects were observed on neurobehavioral development.

8.5 Geriatric Use

Clinical studies of dimethyl fumarate (the prodrug of BAFIERTAM) and of BAFIERTAM did not include sufficient numbers of patients aged 65 and over to determine whether they respond differently from younger patients.

11 DESCRIPTION

BAFIERTAM contains the active ingredient monomethyl fumarate, which is an unsaturated monomethyl ester. It is also known by its chemical name, fumaric acid monomethyl ester, (C5H6O4). It has the following structure:

Monomethyl fumarate is a white to off-white powder that is highly soluble in water with a molecular mass of 130.10.

BAFIERTAM is provided as soft gelatin delayed-release capsules for oral administration, containing 95 mg of monomethyl fumarate consisting of the following inactive ingredients:

Glyceryl caprylate/caprate, lactic acid, polyoxyl 40 hydrogenated castor oil and povidone K30. The capsule shell, printed with black ink, contains the following inactive ingredients: ammonium hydroxide, butyl alcohol, ferrosoferric oxide, isopropyl alcohol, gelatin, propylene glycol, shellac, solution of sorbitans and sorbitol and titanium dioxide. The coating system includes the following inactive ingredients: colloidal anhydrous silica, GMCC Type 1 mono and di-glycerides, hypromellose type 2910, methacrylic acid and ethyl acrylate copolymer, polyethylene glycol (MW=400), polyvinyl alcohol part hydrolyzed, sodium bicarbonate, sodium lauryl sulfate, talc, titanium dioxide and triethyl citrate.

12 CLINICAL PHARMACOLOGY

12.1 Mechanism of Action

The mechanism by which monomethyl fumarate (MMF) exerts its therapeutic effect in multiple sclerosis is unknown. MMF has been shown to activate the Nuclear factor (erythroid-derived 2) like 2 (Nrf2) pathway in vitro and in vivo in animals and humans. The Nrf2 pathway is involved in the cellular response to oxidative stress. MMF has been identified as a nicotinic acid receptor agonist in vitro.

12.2 Pharmacodynamics

Potential to prolong the QT interval

In a placebo controlled thorough QT study performed in healthy subjects with dimethyl fumarate [the prodrug of BAFIERTAM], there was no evidence that dimethyl fumarate caused QT interval prolongation of clinical significance (i.e., the upper bound of the 90% confidence interval for the largest placebo-adjusted, baseline-corrected QTc was below 10 ms).

12.3 Pharmacokinetics

Pharmacokinetics of monomethyl fumarate have previously been characterized after oral administration of its prodrug, dimethyl fumarate, as delayed-release capsules, in healthy subjects and subjects with multiple sclerosis. After oral administration, dimethyl fumarate undergoes rapid presystemic hydrolysis by esterases and is converted to its active metabolite, monomethyl fumarate (MMF). Additional pharmacokinetic data of monomethyl fumarate were obtained after oral administration of BAFIERTAM, the monomethyl fumarate delayed-release capsules, in healthy subjects.

Absorption

Following oral administration of BAFIERTAM 190 mg (two 95 mg monomethyl fumarate delayed-release capsules) under fasting conditions, the median Tmax of MMF is 4.03 hours; and the peak plasma concentration (Cmax) and overall exposure (AUC) of monomethyl fumarate are bioequivalent to those after oral administration of 240 mg dimethyl fumarate delayed-release capsule.

A high-fat, high-calorie meal did not significantly affect the overall monomethyl fumarate plasma exposure (AUC), but decreased the Cmax of MMF by 20%, with prolonged absorption. The median Tmax of MMF was delayed from approximately 4.0 hours to 11 hours by a high fat meal.

Distribution

From studies with dimethyl fumarate (the prodrug of BAFIERTAM), it is shown that the apparent volume of distribution of MMF varies between 53 and 73 L in healthy subjects. Human plasma protein binding of MMF is 27-45% and independent of concentration.

Elimination

Metabolism

In humans, metabolism of MMF occurs through the tricarboxylic acid (TCA) cycle, with no involvement of the cytochrome P450 (CYP450) system. MMF, fumaric and citric acid, and glucose are the major metabolites of MMF in plasma.

Excretion

From studies with dimethyl fumarate (the prodrug of BAFIERTAM), exhalation of CO2 is the primary route of elimination, accounting for approximately 60% of the dimethyl fumarate dose. Renal and fecal elimination are minor routes of elimination for MMF, accounting for 16% and 1% of the dimethyl fumarate dose, respectively. Trace amounts of unchanged MMF were present in urine.

The plasma half-life of MMF is approximately 0.5 hour and no circulating MMF is present at 24 hours in the majority of individuals following oral administration of BAFIERTAM 190 mg (two 95 mg monomethyl fumarate delayed-release capsules) under fasting conditions. Accumulation of MMF does not occur with multiple doses of dimethyl fumarate.

Specific Populations

Body weight, gender, and age differences do not require dosage adjustment.

No studies have been conducted in subjects with hepatic or renal impairment. However, neither condition would be expected to affect plasma exposure to MMF and therefore, no dosage adjustment is necessary.

Drug Interaction Studies

No potential drug interactions with dimethyl fumarate or MMF were identified in in vitro CYP inhibition and induction studies, or in P-glycoprotein studies. Single doses of interferon beta-1a or glatiramer acetate did not alter the pharmacokinetics of MMF. Aspirin, when administered approximately 30 minutes before dimethyl fumarate, did not alter the pharmacokinetics of MMF.

Oral Contraceptives

The coadministration of the prodrug of BAFIERTAM, dimethyl fumarate, with a combined oral contraceptive (norelgestromin and ethinyl estradiol) did not elicit any relevant effects in oral contraceptives exposure. No interaction studies have been performed with oral contraceptives containing other progestogens.

13 NONCLINICAL TOXICOLOGY

13.1 Carcinogenesis, Mutagenesis, Impairment of Fertility

Carcinogenesis

Carcinogenicity studies of dimethyl fumarate (DMF) were conducted in mice and rats. In mice, oral administration of DMF (0, 25, 75, 200, and 400 mg/kg/day) for up to two years resulted in an increase in nonglandular stomach (forestomach) and kidney tumors: squamous cell carcinomas and papillomas of the forestomach in males and females at 200 and 400 mg/kg/day; leiomyosarcomas of the forestomach at 400 mg/kg/day in males and females; renal tubular adenomas and carcinomas at 200 and 400 mg/kg/day in males; and renal tubule adenomas at 400 mg/kg/day in females. Plasma MMF exposure (AUC) at the highest dose not associated with tumors in mice (75 mg/kg/day) was similar to that in humans at the recommended human dose (RHD) of MMF (380 mg/day).

In rats, oral administration of DMF (0, 25, 50, 100, and 150 mg/kg/day) for up to two years resulted in increases in squamous cell carcinomas and papillomas of the forestomach at all doses tested in males and females, and in testicular interstitial (Leydig) cell adenomas at 100 and 150 mg/kg/day. Plasma MMF AUC at the lowest dose tested was lower than that in humans at the RHD of MMF.

Mutagenesis

Monomethyl fumarate (MMF) was not mutagenic in the in vitro bacterial reverse mutation (Ames) assay. MMF was clastogenic in the in vitro chromosomal aberration assay in human peripheral blood lymphocytes in the absence of metabolic activation. DMF was not clastogenic in the in vivo micronucleus assay in the rat.

Impairment of Fertility

In male rats, oral administration of DMF (0, 75, 250, and 375 mg/kg/day) prior to and throughout the mating period had no effect on fertility; however, increases in non-motile sperm were observed at the mid and high doses. The no-effect dose for adverse effects on sperm is similar to the recommended human dose (RHD) of DMF (480 mg/day) on a body surface area (mg/m^2) basis. MMF (380 mg/day) is bioequivalent to DMF (480 mg/day).

In female rats, oral administration of DMF (0, 20, 100, and 250 mg/kg/day) prior to and during mating and continuing to gestation day 7 caused disruption of the estrous cycle and increases in embryolethality at the highest dose tested. The highest dose not associated with adverse effects (100 mg/kg/day) is twice the RHD for DMF on a mg/m^2 basis. MMF (380 mg/day) is bioequivalent to DMF (480 mg/day).

Testicular toxicity (germinal epithelial degeneration, atrophy, hypospermia, and/or hyperplasia) was observed at clinically relevant doses in mice, rats, and dogs in subchronic and chronic oral toxicity studies of DMF, and in a chronic oral toxicity study evaluating a combination of four fumaric acid esters (including DMF) in rats.

13.2 Animal Toxicology and/or Pharmacology

Kidney toxicity was observed after repeated oral administration of dimethyl fumarate (DMF) in mice, rats, dogs, and monkeys. Renal tubule epithelia regeneration, suggestive of tubule epithelial injury, was observed in all species. Renal tubular hyperplasia was observed in rats with dosing for up to two years. Cortical atrophy and interstitial fibrosis were observed in dogs and monkeys at doses above 5 mg/kg/day. In monkeys, the highest dose tested (75 mg/kg/day) was associated with single cell necrosis and multifocal and diffuse interstitial fibrosis, indicating irreversible loss of renal tissue and function. In dogs and monkeys, the 5 mg/kg/day dose was associated with plasma MMF exposures less than or similar to that in humans at the recommended human dose (RHD) of MMF (380 mg/day).

A dose-related increase in incidence and severity of retinal degeneration was observed in mice following oral administration of DMF for up to two years at doses above 75 mg/kg/day, a dose associated with plasma MMF exposure (AUC) similar to that in humans at the RHD of MMF (380 mg/day).

14 CLINICAL STUDIES

The efficacy of BAFIERTAM is based upon bioavailability studies in healthy subjects comparing oral dimethyl fumarate delayed-release capsules to BAFIERTAM delayed-release capsules [see Clinical Pharmacology (12.3)].

The clinical studies described below were conducted using dimethyl fumarate.

The efficacy and safety of dimethyl fumarate were demonstrated in two studies (Studies 1 and 2) that evaluated dimethyl fumarate taken either twice or three times a day in patients with relapsing-remitting multiple sclerosis (RRMS). The starting dose for dimethyl fumarate was 120 mg twice or three times a day for the first 7 days, followed by an increase to 240 mg twice or three times a day. Both studies included patients who had experienced at least 1 relapse over the year preceding the trial or had a brain Magnetic Resonance Imaging (MRI) scan demonstrating at least one gadolinium-enhancing (Gd+) lesion within 6 weeks of randomization. The Expanded Disability Status Scale (EDSS) was also assessed and patients could have scores ranging from 0 to 5. Neurological evaluations were performed at baseline, every 3 months, and at the time of suspected relapse. MRI evaluations were performed at baseline, month 6, and year 1 and 2 in a subset of patients (44% in Study 1 and 48% in Study 2).

Study 1: Placebo-Controlled Trial in RRMS

Study 1 was a 2-year randomized, double-blind, placebo-controlled study in 1234 patients with RRMS. The primary endpoint was the proportion of patients relapsed at 2 years. Additional endpoints at 2 years included the number of new or newly enlarging T2 hyperintense lesions, number of new T1 hypointense lesions, number of Gd+ lesions, annualized relapse rate (ARR), and time to confirmed disability progression. Confirmed disability progression was defined as at least a 1 point increase from baseline EDSS (1.5 point increase for patients with baseline EDSS of 0) sustained for 12 weeks.

Patients were randomized to receive dimethyl fumarate 240 mg twice a day (n=410), dimethyl fumarate 240 mg three times a day (n=416), or placebo (n=408) for up to 2 years. The median age was 39 years, median time since diagnosis was 4 years, and median EDSS score at baseline was 2. The median time on study drug for all treatment arms was 96 weeks. The percentages of patients who completed 96 weeks on study drug per treatment group were 69% for patients assigned to dimethyl fumarate 240 mg twice a day, 69% for patients assigned to dimethyl fumarate 240 mg three times a day, and 65% for patients assigned to placebo groups.

Dimethyl fumarate had a statistically significant effect on all of the endpoints described above and the 240 mg three times daily dose showed no additional benefit over the dimethyl fumarate 240 mg twice daily dose. The results for this study (240 mg twice a day vs. placebo) are shown in Table 2 and Figure 1.

Table 2: Clinical and MRI Results of Study 1
 | Dimethyl Fumarate 240 mg BID | Placebo | P-value
Clinical Endpoints | N=410 | N=408
Proportion relapsing (primary endpoint) Relative risk reduction | 27% 49% | 46% | <0.0001
Annualized relapse rate | 0.172 | 0.364 | <0.0001
Relative reduction | 53 %
Proportion with disability progression | 16% | 27% | 0.0050
Relative risk reduction | 38%
MRI Endpoints | N=152 | N=165
Mean number of new or newly enlarging | 2.6 | 17 | <0.0001
T2 lesions over 2 years Percentage of subjects with no new or newly enlarging lesions | 45% | 27%
Number of Gd+ lesions at 2 years | 0.1 (0) | 1.8 (0)
Mean (median) Percentage of subjects with 0 lesions | 93% | 62%
1 lesion | 5% | 10%
2 lesions | <1% | 8%
3 to 4 lesions | 0 | 9%
5 or more lesions | <1% | 11%
Relative odds reduction (percentage) | 90 % |  | <0.0001
Mean number of new T1 hypointense lesions over 2 years | 1.5 | 5.6 | <0.0001

Figure 1: Time to 12-Week Confirmed Progression of Disability (Study 1)

Study 2: Placebo-Controlled Trial in RRMS

Study 2 was a 2-year multicenter, randomized, double-blind, placebo-controlled study that also included an open-label comparator arm in patients with RRMS. The primary endpoint was the annualized relapse rate at 2 years. Additional endpoints at 2 years included the number of new or newly enlarging T2 hyperintense lesions, number of T1 hypointense lesions, number of Gd+ lesions, proportion of patients relapsed, and time to confirmed disability progression as defined in Study 1.

Patients were randomized to receive dimethyl fumarate 240 mg twice a day (n=359), dimethyl fumarate 240 mg three times a day (n=345), an open-label comparator (n=350), or placebo (n=363) for up to 2 years. The median age was 37 years, median time since diagnosis was 3 years, and median EDSS score at baseline was 2.5. The median time on study drug for all treatment arms was 96 weeks. The percentages of patients who completed 96 weeks on study drug per treatment group were 70% for patients assigned to dimethyl fumarate 240 mg twice a day, 72% for patients assigned to dimethyl fumarate 240 mg three times a day, and 64% for patients assigned to placebo groups.

Dimethyl fumarate had a statistically significant effect on the relapse and MRI endpoints described above. There was no statistically significant effect on disability progression. The dimethyl fumarate 240 mg three times daily dose resulted in no additional benefit over the dimethyl fumarate 240 mg twice daily dose. The results for this study (240 mg twice a day vs. placebo) are shown in Table 3.

Table 3: Clinical and MRI Results of Study 2
 | Dimethyl Fumarate 240 mg BID | Placebo | P-value
Clinical Endpoints | N=359 | N=363
Annualized relapse rate | 0.224 | 0.401 | <0.0001
Relative reduction | 44%
Proportion relapsing | 29% | 41% | 0.0020
Relative risk reduction | 34%
Proportion with disability progression | 13% | 17% | 0.25
Relative risk reduction | 21%
MRI Endpoints | N=147 | N=144
Mean number of new or newly enlarging | 5.1 | 17.4 | <0.0001
T2 lesions over 2 years Percentage of subjects with no new or newly enlarging lesions | 27 % | 12 %
Number of Gd+ lesions at 2 years Mean (median) | 0.5 (0.0) | 2.0 (0.0)
Percentage of subjects with 0 lesions | 80% | 61%
1 lesion | 11% | 17%
2 lesions | 3% | 6%
3 to 4 lesions | 3% | 2%
5 or more lesions | 3% | 14%
Relative odds reduction (percentage) | 74 % |  | <0.0001
Mean number of new T1 hypointense lesions over 2 years | 3.0 | 7.0 | <0.0001

16 HOW SUPPLIED/STORAGE AND HANDLING

16.1 How Supplied

BAFIERTAM is available as soft gelatin delayed-release capsules containing 95 mg of monomethyl fumarate. The 95 mg capsules are white, opaque, oval, and coated with “95” printed in black ink on the body. BAFIERTAM is available as follows:

95 mg capsules: bottle of 120 capsules (NDC 69387-001-01).

16.2 Storage and Handling

Unopened Bottle

Store unopened bottles in refrigerator at 2°C to 8°C (35°F to 46°F). Do not freeze. Under these conditions, BAFIERTAM is stable until the expiration date indicated on the package.

Opened Bottle

Opened bottles may be stored at 20°C to 25°C (68°F to 77°F); excursions between 15°C and 30°C (59°F and 86°F) permitted [see USP Controlled Room Temperature]. Protect the capsules from light. Store in original container. Under these conditions, BAFIERTAM is stable for 3 months.

Capsules may become deformed if kept at high temperatures.

17 PATIENT COUNSELING INFORMATION

Advise the patient to read the FDA-approved patient labeling (Patient Information).

Dosage

Inform patients that they will be provided one strength of BAFIERTAM when starting treatment: take one capsule for the 7 day starter dose and two capsules for the maintenance dose, both to be taken twice daily. Inform patients to swallow BAFIERTAM capsules whole and intact. Inform patients to not crush, chew, or mix capsule contents with food. Inform patients that BAFIERTAM can be taken with or without food [see Dosage and Administration (2.2, 2.3)].

Anaphylaxis and Angioedema

Advise patients to discontinue BAFIERTAM and seek medical care if they develop signs and symptoms of anaphylaxis or angioedema [see Warnings and Precautions (5.1)].

Progressive Multifocal Leukoencephalopathy

Inform patients that progressive multifocal leukoencephalopathy (PML) has occurred in patients who received dimethyl fumarate (the prodrug of monomethyl fumarate). Inform the patient that PML is characterized by a progression of deficits and usually leads to death or severe disability over weeks or months. Instruct the patient of the importance of contacting their healthcare provider if they develop any symptoms suggestive of PML. Inform the patient that typical symptoms associated with PML are diverse, progress over days to weeks, and include progressive weakness on one side of the body or clumsiness of limbs, disturbance of vision, and changes in thinking, memory, and orientation leading to confusion and personality changes [see Warnings and Precautions (5.2)].

Herpes Zoster and Other Serious Opportunistic Infections

Inform patients that herpes zoster and other serious opportunistic infections have occurred in patients who received dimethyl fumarate. Instruct the patient of the importance of contacting their healthcare provider if they develop any signs or symptoms associated with herpes zoster or other serious opportunistic infections [see Warnings and Precautions (5.3)].

Lymphocyte Counts

Inform patients that BAFIERTAM may decrease lymphocyte counts. A blood test should be obtained before they start therapy. Blood tests are also recommended after 6 months of treatment, every 6 to 12 months thereafter, and as clinically indicated [see Warnings and Precautions (5.4), Adverse Reactions (6.1)].

Liver Injury

Inform patients that BAFIERTAM may cause liver injury. Instruct patients treated with BAFIERTAM to report promptly to their healthcare provider any symptoms that may indicate liver injury, including fatigue, anorexia, right upper abdominal discomfort, dark urine, or jaundice. A blood test should be obtained before patients start therapy and during treatment, as clinically indicated [see Warnings and Precautions (5.5)].

Flushing

Inform patients that flushing is one of the most common reactions, especially at the initiation of therapy, and may decrease over time. Advise patients to contact their healthcare provider if they experience persistent and/or severe flushing. Advise patients experiencing flushing that taking a non-enteric coated aspirin prior to taking BAFIERTAM may help [see Adverse Reactions (6.1)].

Gastrointestinal (GI) Reactions

Inform patients that GI events (abdominal pain, diarrhea, and nausea) are some of the most common adverse reactions, especially at the initiation of therapy, and may decrease over time. Some patients may experience more severe GI events. Advise patients to immediately contact their healthcare provider and discontinue BAFIERTAM if they experience gastrointestinal bleeding (e.g., rectal bleeding, bloody diarrhea, hematemesis) or other serious gastrointestinal adverse events (e.g., severe abdominal pain, severe vomiting and/or diarrhea) [see Warnings and Precautions (5.7)].

Pregnancy and Pregnancy Registry

Instruct patients that if they are pregnant or plan to become pregnant while taking BAFIERTAM they should inform their healthcare provider. Advise patients that there is a pregnancy registry that monitors pregnancy outcomes in women exposed to BAFIERTAM during pregnancy, and they can be enrolled by calling 1-866-MMF-95MG (1-866-663-9564) [see Use in Specific Populations (8.1)].

Manufactured by:

Banner Life Sciences LLC, High Point, NC 27265

BAFIERTAM is a registered trademark of Banner Life Sciences LLC.

© Banner Life Sciences 2024

Marketed by:
Cycle Pharmaceuticals Ltd
The Broers Building
21 JJ Thomson Ave
Cambridge, CB3 0FA, United Kingdom

Patented: see www.cyclepharma.com/product-patent-information

Patient Information
BAFIERTAM®
(bah”feer'tam)
(monomethyl fumarate)
delayed-release capsules, for oral use

What is BAFIERTAM?

- BAFIERTAM is a prescription medicine used to treat relapsing forms of multiple sclerosis (MS), to include clinically isolated syndrome, relapsing-remitting disease, and active secondary progressive disease, in adults.
- It is not known if BAFIERTAM is safe and effective in children.

Do not take BAFIERTAM if you:

- have had an allergic reaction (such as welts, hives, swelling of the face, lips, mouth or tongue, or difficulty breathing) to monomethyl fumarate, dimethyl fumarate, diroximel fumarate, or any of the ingredients in BAFIERTAM. See “WHAT ARE THE INGREDIENTS IN BAFIERTAM?” for a complete list of ingredients.
- are taking dimethyl fumarate or diroximel fumarate.

Before taking and while you take BAFIERTAM, tell your doctor about all of your medical conditions, including if you:

- have liver problems
- have or have had low white blood cell counts or an infection
- are pregnant or plan to become pregnant. It is not known if BAFIERTAM will harm your unborn baby. You and your doctor will have to decide if you should take BAFIERTAM while you are pregnant or if you plan to become pregnant.
  - Pregnancy Registry: There is a pregnancy registry for women who take BAFIERTAM during pregnancy. If you become pregnant while taking BAFIERTAM, talk to your doctor about enrolling in the pregnancy registry. You can enroll or your healthcare provider can enroll you by calling 1-866-663-95MG (1-866-663-9564). The purpose of this registry is to collect information about the health of you and your baby.
- are breastfeeding or plan to breastfeed. It is not known if BAFIERTAM passes into your breast milk. Talk to your healthcare provider about the best way to feed your baby while using BAFIERTAM.

Tell your doctor about all the medicines you take including prescription and over-the-counter medicines, vitamins, and herbal supplements.

How should I take BAFIERTAM?

- Take BAFIERTAM exactly as your doctor tells you to take it.
- You will be given 1 strength of BAFIERTAM when starting your treatment.
- The recommended starting dose is one 95 mg capsule taken by mouth 2 times a day for 7 days.
- The recommended dose after 7 days is two 95 mg capsules taken by mouth 2 times a day.
- BAFIERTAM can be taken with or without food.
- Swallow BAFIERTAM capsules whole and intact. Do not crush, chew, or mix the contents with food.
- If you take too much BAFIERTAM, call your doctor or go to the nearest hospital emergency room right away.

What are the possible side effects of BAFIERTAM?
BAFIERTAM may cause serious side effects including:

- allergic reaction (such as welts, hives, swelling of the face, lips, mouth or tongue, or difficulty breathing).
- Stop taking BAFIERTAM and get emergency medical help right away if you get any of these symptoms.
- PML (progressive multifocal leukoencephalopathy), a rare brain infection that usually leads to death or severe disability over a period of weeks or months. Tell your doctor right away if you get any of these symptoms of PML:

- weakness on one side of the body that gets worse
- vision problems
- confusion

- clumsiness in your arms or legs
- changes in thinking and memory
- personality changes

- herpes zoster infections (shingles), including central nervous system infections
- other serious infections
- decreases in your white blood cell count: Your doctor should do a blood test to check your white blood cell count before you start treatment with BAFIERTAM and while you are on therapy. You should have blood tests after 6 months of treatment and every 6 to 12 months after that.
- liver problems: Your doctor should do blood tests to check your liver function before you start taking BAFIERTAM and during treatment if needed. Tell your doctor right away if you get any of these symptoms of a liver problem during treatment:
  - severe tiredness
  - loss of appetite
  - pain on the right side of your stomach
  - have dark or brown (tea color) urine
  - yellowing of your skin or the white part of your eyes
- serious gastrointestinal problems, including bleeding, ulcers, blockage, and tears (perforation) of the stomach or intestines. Tell your healthcare provider right away if you have any of these symptoms during treatment:
  - Stomach-area pain that does not go away
  - Bright red or black stools (that look like tar)
  - Severe vomiting
  - Severe diarrhea
  - Coughing up blood or blood clots
  - Vomiting blood or your vomit looks like “coffee grounds”

The most common side effects of BAFIERTAM include:

- flushing, redness, itching, or rash
- nausea, vomiting, diarrhea, stomach pain, or indigestion. These events can be serious in some patients (see “BAFIERTAM may cause serious side effects including,” above).
- Flushing and stomach problems are the most common reactions, especially at the start of treatment, and may decrease over time. Call your doctor if you have any of these symptoms and they bother you or do not go away. Speak to your doctor about taking aspirin to reduce flushing symptoms, as this has been reported to help.

These are not all the possible side effects of BAFIERTAM. Call your doctor for medical advice about side effects. You may report side effects to FDA at 1-800-FDA-1088.
For more information go to dailymed.nlm.nih.gov.

How should I store BAFIERTAM?

- Store BAFIERTAM in the original container.
- Protect the capsules from light.
- Store unopened bottles of BAFIERTAM in the refrigerator between 35°F to 46°F (2°C to 8°C).
- Store opened bottles of BAFIERTAM at room temperature between 68°F to 77°F (20°C to 25°C). BAFIERTAM capsules are good for 3 months after the bottle is opened. Throw away BAFIERTAM capsules if the bottle has been opened for more than 3 months.
- Capsules may become deformed if kept at high temperatures.
- Keep BAFIERTAM and all medicines out of the reach of children.

General Information about the safe and effective use of BAFIERTAM
Medicines are sometimes prescribed for purposes other than those listed in this Patient Information. Do not use BAFIERTAM for a condition for which it was not prescribed. Do not give BAFIERTAM to other people, even if they have the same symptoms that you have. It may harm them.
If you would like more information, talk to your doctor or pharmacist. You can ask your pharmacist or doctor for information about BAFIERTAM that is written for health professionals.

What are the ingredients in BAFIERTAM?
Active ingredient: monomethyl fumarate
Inactive ingredients: Glyceryl caprylate/caprate, lactic acid, polyoxyl 40 hydrogenated castor oil and povidone K30. The capsule shell, printed with black ink, contains the following inactive ingredients: ammonium hydroxide, butyl alcohol, ferrosoferric oxide, isopropyl alcohol, gelatin, propylene glycol, shellac, solution of sorbitans and sorbitol and titanium dioxide. The coating system includes the following inactive ingredients: colloidal anhydrous silica, GMCC Type 1 mono and di-glycerides, hypromellose type 2910, methacrylic acid and ethyl acrylate copolymer, polyethylene glycol (MW=400), polyvinyl alcohol part hydrolyzed, sodium bicarbonate, sodium lauryl sulfate, talc, titanium dioxide and triethyl citrate.
Manufactured by: Banner Life Sciences LLC, High Point, NC 27265, www.BAFIERTAM.com or call 1-866-MMF-95MG.

This Patient Information has been approved by the U.S. Food and Drug Administration. Revised: 12/2023

Principal Display Panel – Bottle Label

69387-001-01

120 capsules

Rx only

Bafiertam®

(monomethyl fumarate)

Delayed-release capsules

95 mg

Dispense in Original Package.

Swallow capsules whole.